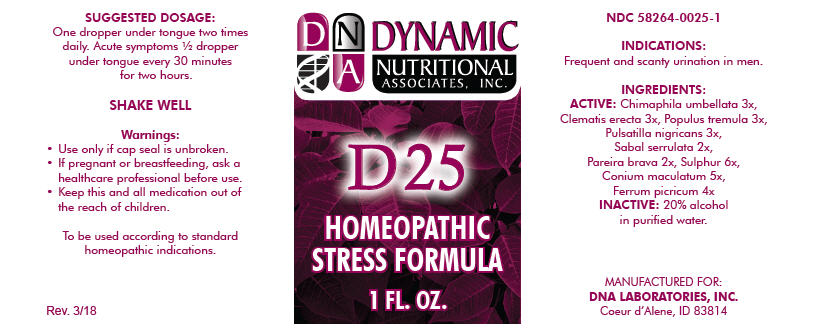 DRUG LABEL: D-25
NDC: 58264-0025 | Form: SOLUTION/ DROPS
Manufacturer: DNA Labs, Inc.
Category: homeopathic | Type: HUMAN OTC DRUG LABEL
Date: 20250113

ACTIVE INGREDIENTS: CHIMAPHILA UMBELLATA 3 [hp_X]/1 mL; CLEMATIS RECTA FLOWERING TOP 3 [hp_X]/1 mL; POPULUS TREMULA WHOLE 3 [hp_X]/1 mL; ANEMONE PRATENSIS 3 [hp_X]/1 mL; SAW PALMETTO 2 [hp_X]/1 mL; CHONDRODENDRON TOMENTOSUM ROOT 2 [hp_X]/1 mL; SULFUR 6 [hp_X]/1 mL; CONIUM MACULATUM FLOWERING TOP 5 [hp_X]/1 mL; FERRIC PICRATE 4 [hp_X]/1 mL
INACTIVE INGREDIENTS: ALCOHOL; WATER

D-25

NDC 58264-0025-1

INDICATIONS

PURPOSE

Frequent and scanty urination in men.

INGREDIENTS

ACTIVE

Chimaphila umbellata 3x, Clematis erecta 3x, Populus tremula 3x, Pulsatilla nigricans 3x, Sabal serrulata 2x, Pareira brava 2x, Sulphur 6x, Conium maculatum 5x, Ferrum picricum 4x

INACTIVE

20% alcohol in purified water.

SUGGESTED DOSAGE

One dropper under tongue two times daily. Acute symptoms ½ dropper under tongue every 30 minutes for two hours.

STORAGE AND HANDLING

SHAKE WELL

Warnings

- Use only if cap seal is unbroken.

PREGNANCY OR BREAST FEEDING

- If pregnant or breastfeeding, ask a healthcare professional before use.

KEEP OUT OF REACH OF CHILDREN

- Keep this and all medication out of the reach of children.

To be used according to standard homeopathic indications.

PRINCIPAL DISPLAY PANEL - 1 FL. OZ. Bottle Label

DYNAMIC
NUTRITIONAL
ASSOCIATES, INC.

D 25

HOMEOPATHIC
STRESS FORMULA

1 FL. OZ.